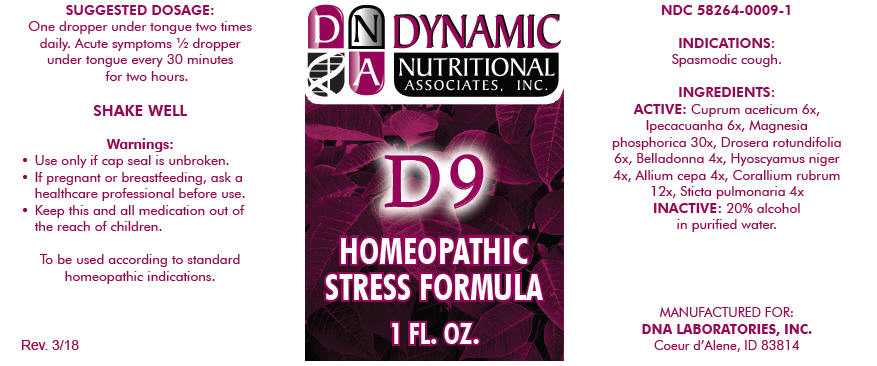 DRUG LABEL: D-9
NDC: 58264-0009 | Form: SOLUTION
Manufacturer: DNA Labs, Inc.
Category: homeopathic | Type: HUMAN OTC DRUG LABEL
Date: 20250113

ACTIVE INGREDIENTS: CUPRIC ACETATE 6 [hp_X]/1 mL; IPECAC 6 [hp_X]/1 mL; MAGNESIUM PHOSPHATE, DIBASIC TRIHYDRATE 30 [hp_X]/1 mL; DROSERA ROTUNDIFOLIA 6 [hp_X]/1 mL; ATROPA BELLADONNA 4 [hp_X]/1 mL; HYOSCYAMUS NIGER 4 [hp_X]/1 mL; ONION 4 [hp_X]/1 mL; CORALLIUM RUBRUM EXOSKELETON 12 [hp_X]/1 mL; LOBARIA PULMONARIA 4 [hp_X]/1 mL
INACTIVE INGREDIENTS: ALCOHOL; WATER

D-9

NDC 58264-0009-1

INDICATIONS

PURPOSE

Spasmodic cough.

INGREDIENTS

ACTIVE

Cuprum aceticum 6x, Ipecacuanha 6x, Magnesia phosphorica 30x, Drosera rotundifolia 6x, Belladonna 4x, Hyoscyamus niger 4x, Allium cepa 4x, Corallium rubrum 12x, Sticta pulmonaria 4x

INACTIVE

20% alcohol in purified water.

SUGGESTED DOSAGE

One dropper under tongue two times daily. Acute symptoms ½ dropper under tongue every 30 minutes for two hours.

STORAGE AND HANDLING

SHAKE WELL

Warnings

- Use only if cap seal is unbroken.

PREGNANCY OR BREAST FEEDING

- If pregnant or breastfeeding, ask a healthcare professional before use.

KEEP OUT OF REACH OF CHILDREN

- Keep this and all medication out of the reach of children.

To be used according to standard homeopathic indications.

PRINCIPAL DISPLAY PANEL - 1 FL. OZ. Bottle Label

DYNAMIC
NUTRITIONAL
ASSOCIATES, INC.

D 9

HOMEOPATHIC
STRESS FORMULA

1 FL. OZ.